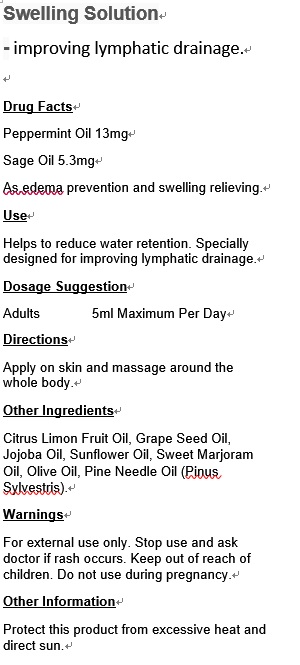 DRUG LABEL: Swelling Solution
NDC: 70470-8003 | Form: OIL
Manufacturer: PHYTOPIA CO., LTD.
Category: otc | Type: HUMAN OTC DRUG LABEL
Date: 20160501

ACTIVE INGREDIENTS: PEPPERMINT 13 mg/50 mL; SAGE OIL 5.3 mg/50 mL
INACTIVE INGREDIENTS: OLIVE OIL; SWEET MARJORAM OIL; PINE NEEDLE OIL (PINUS SYLVESTRIS); GRAPE SEED OIL; JOJOBA OIL; SUNFLOWER OIL; CITRUS LIMON FRUIT OIL

Drug Facts

Peppermint Oil 13mg

Sage Oil 5.3mg

As.edema prevention and swelling relieving.

Use

Helps to reduce water retention. Specially designed for improving lymphatic drainage.

Dosage Suggestion

Adults 5ml Maximum Per Day

Directions

Apply on skin and massage around the whole body.

INACTIVE INGREDIENT

Other Ingredients

Citrus Limon Fruit Oil, Grape Seed Oil, Jojoba Oil, Sunflower Oil, Sweet Marjoram Oil, Olive Oil,

Pine Needle Oil (Pinus Sylvestris).

Warnings

For external use only. Stop use and ask doctor if rash occurs. Keep out of reach of children. Do not use during pregnancy.

Warnings

For external use only. Stop use and ask doctor if rash occurs. Keep out of reach of children. Do not use during pregnancy.

Warnings

For external use only. Stop use and ask doctor if rash occurs. Keep out of reach of children. Do not use during pregnancy.

Other Information

Protect this product from excessive heat and direct sun.

PACKAGE LABEL

Swelling Solution- improving lymphatic drainage.